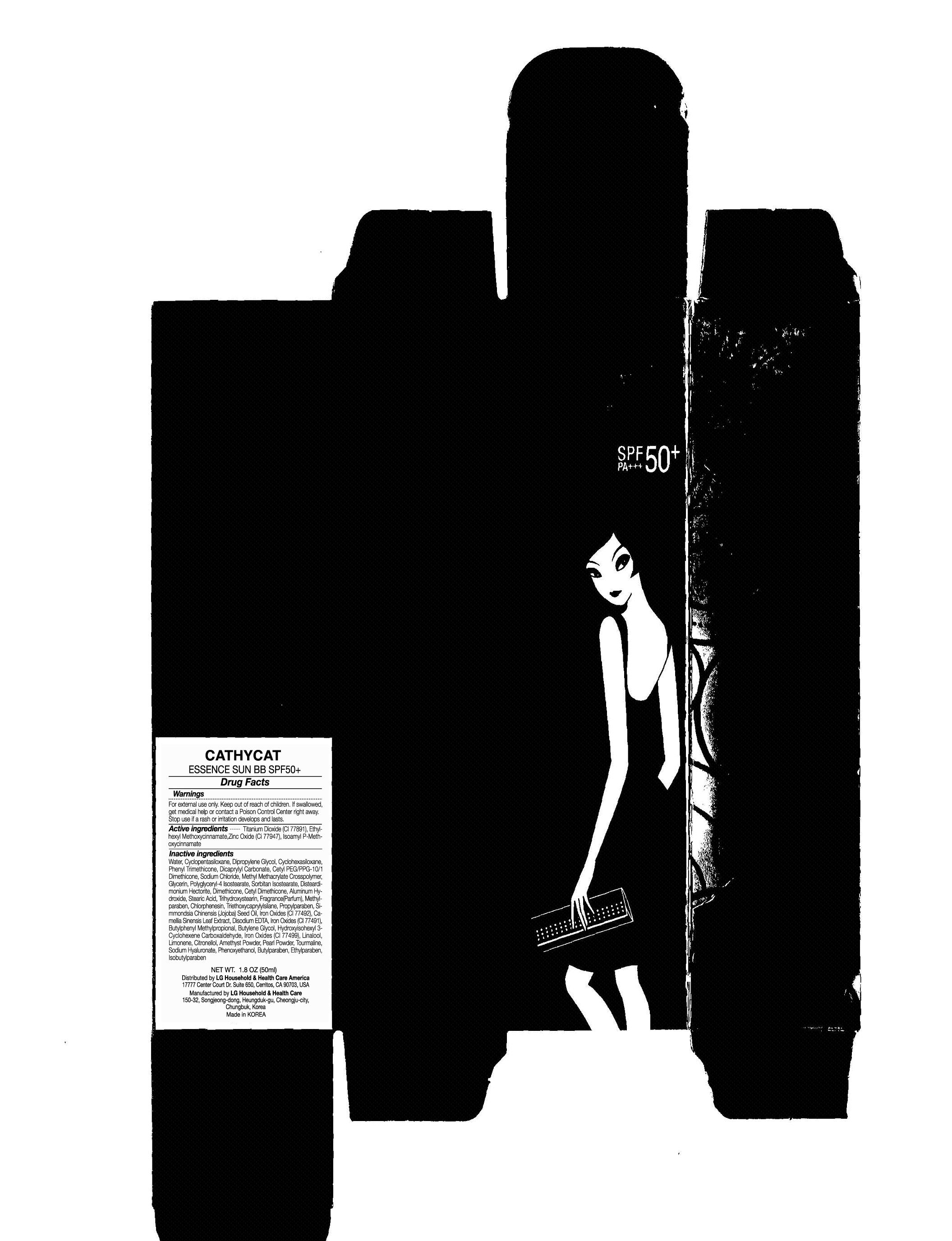 DRUG LABEL: CATHYCAT ESSENCE SUN BB
NDC: 53208-528 | Form: LIQUID
Manufacturer: LG Household and Healthcare, Inc.
Category: otc | Type: HUMAN OTC DRUG LABEL
Date: 20120516

ACTIVE INGREDIENTS: Titanium Dioxide 13.76176 mL/100 mL; OCTINOXATE 7 mL/100 mL; Zinc Oxide 3.92 mL/100 mL; AMILOXATE 1 mL/100 mL
INACTIVE INGREDIENTS: Water; CYCLOMETHICONE 5; Dipropylene Glycol; CYCLOMETHICONE 6; Dicaprylyl Carbonate; Sodium Chloride; METHYL METHACRYLATE; Glycerin; POLYGLYCERYL-4 ISOSTEARATE; Sorbitan; Hectorite; Dimethicone; Aluminum Hydroxide; Stearic Acid; Trihydroxystearin; Methylparaben; CHLORPHENESIN; Triethoxycaprylylsilane; Propylparaben; Iron; GREEN TEA LEAF; EDETATE DISODIUM; Butylphenyl Methylpropional; Butylene Glycol; FERRIC OXIDE RED; LINALOOL, DL-; .BETA.-CITRONELLOL, (R)-; HYALURONATE SODIUM; Phenoxyethanol; Butylparaben; Ethylparaben; Isobutylparaben

Drug Fact

ACTIVE INGREDIENT

Titanium Dioxide 13.76%

OCTINOXATE 7%

Zinc Oxide 3.92%

AMILOXATE 1%

WARNINGS AND PRECAUTIONS

For external use only.

Keep out of reach of children. Is swallowed, get medical help or contact a Poison Control Center right away.

WHEN USING

Keep out of eyes. Rinse with water to remove.